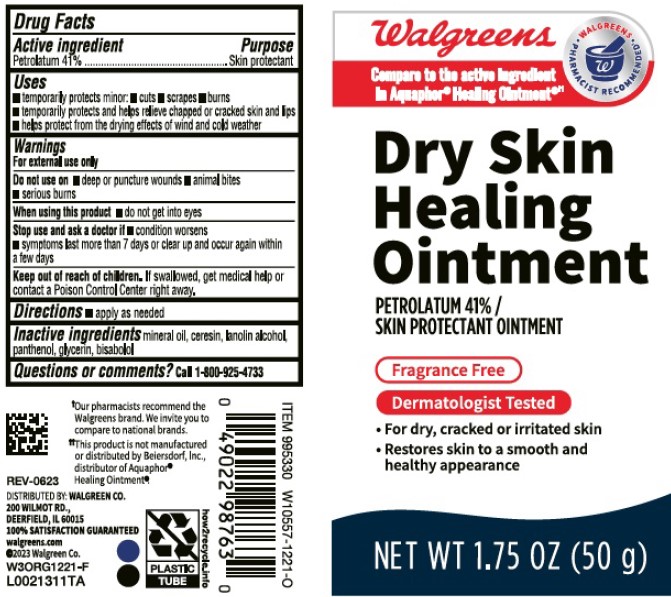 DRUG LABEL: Advanced Healing
NDC: 0363-9247 | Form: OINTMENT
Manufacturer: Walgreen Co.
Category: otc | Type: HUMAN OTC DRUG LABEL
Date: 20260212

ACTIVE INGREDIENTS: PETROLATUM 410 mg/1 g
INACTIVE INGREDIENTS: CERESIN; MINERAL OIL; LANOLIN ALCOHOLS; PANTHENOL; GLYCERIN; LEVOMENOL

Walgreens 247.000/247AA-AC
Healing Ointment for Dry and Cracked Skin

Active ingredient

Petrolaturm 41%

Purpose

Skin protectant

Uses

- temporarily protects minor: •cuts •scrapes burns
- temporarily protects and helps relieve chapped and cracked skin and lips
- helps protect from the drying effects of wind and cold weather

Warnings

For external use only

Do not use on

- deep or puncture wounds
- animal bites
- serious burns

When using this product

- do not get in eyes

Stop use and ask a doctor if

- condition worsens
- symptoms last more than 7 days or clear up and occur again within a few days

Keep out of reach of children.

If swallowed, get medical help or contract a Poison Control Center right away.

Directions

- apply as needed

Inactive ingredients

mineral oil, ceresin, lanolin alcohol, panthenol, glycerin, bisabolol

Questions or comments?

Call 1-800-925-4733

†Our pharmacists recommend the Walgreens brand. We invite you to compare to national brands.

‡This product is not manufactured or distributed by Beiersdorf Inc., distributor of Aquaphor®Healing Ointment®.

ADVERSE REACTION

Distributed by: Walgreen Co.

200 Wilmot Rd.,

Deerfield, IL 60015

100% SATISFACTION GUARANTEED

walgreens.com

©2023 Walgreen Co.

PLASTIC TUBE

how2recycle.info

Principal Panel Display

Walgreens

Walgreens pharmacist recommended†

Compare to the active ingredient Aquaphor® Healing Ointment®‡

Dry Skin Healing Ointment

PETROLATUM 41% /

SKIN PROTECTANT OINTMENT

FRAGRANCE FREE

Dermatologist tested

Skin protectant

- For dry, cracked or irritated skin
- Restores skin to a smooth and healthy appearance

NET WT 1.75 OZ (50 g)